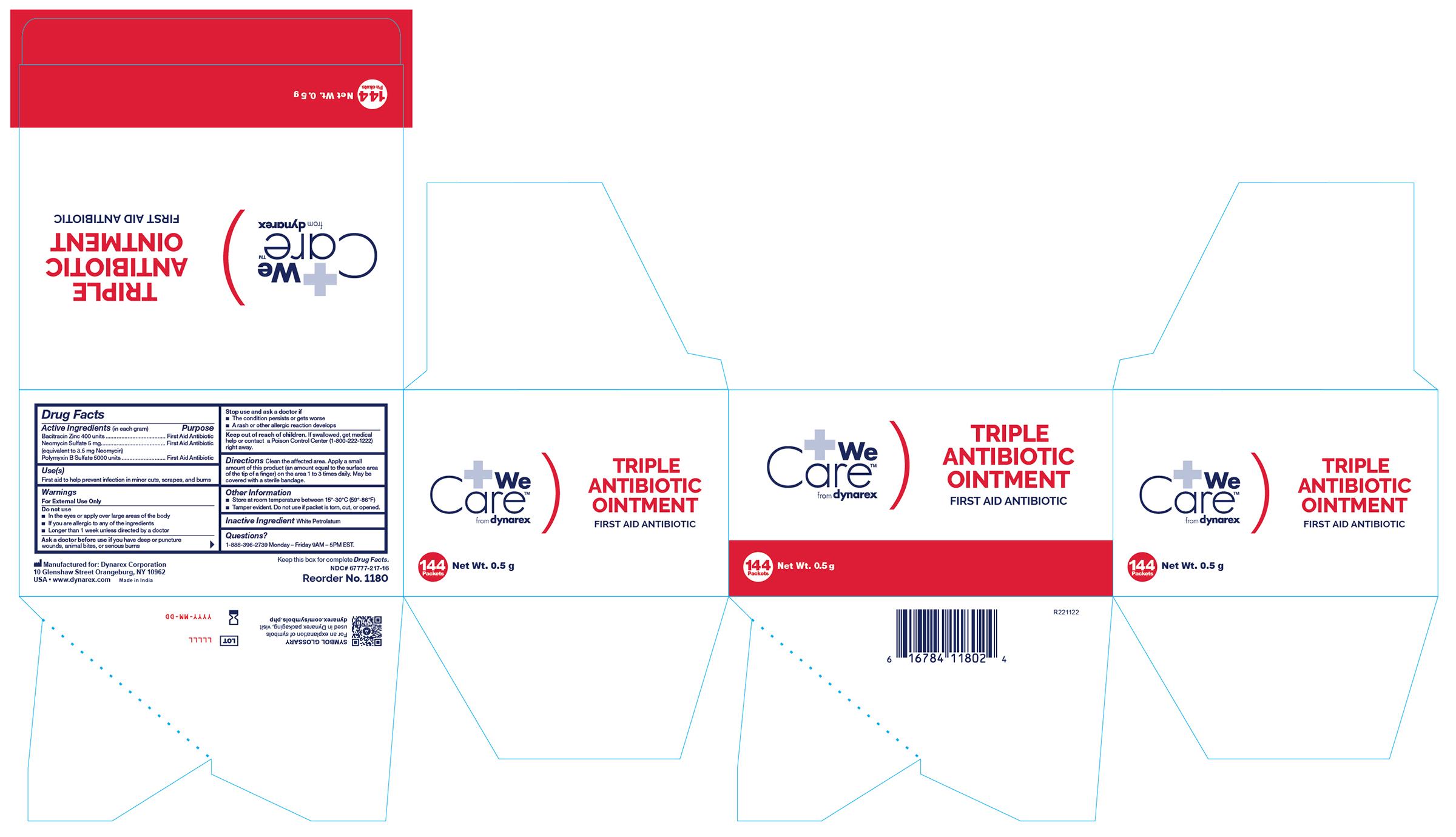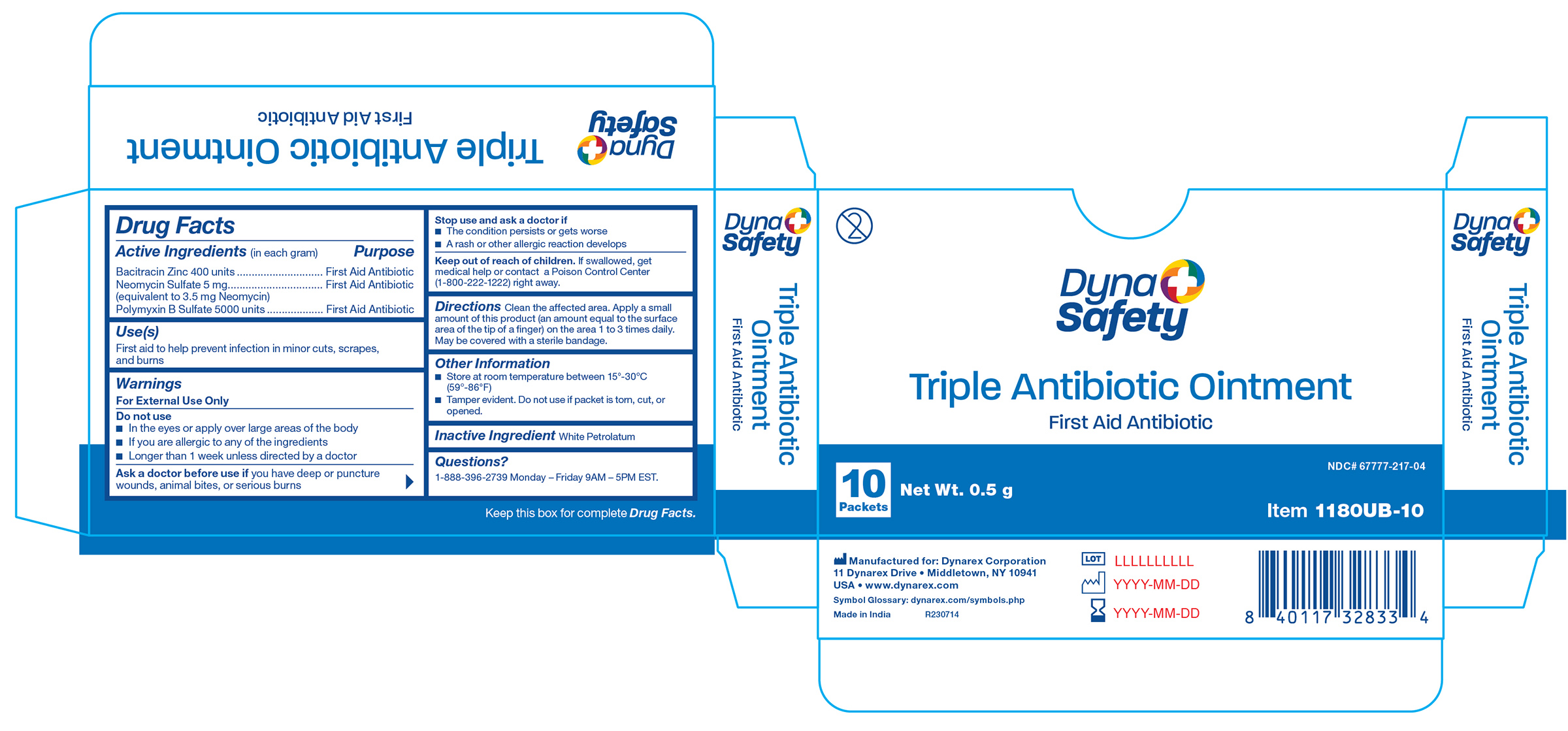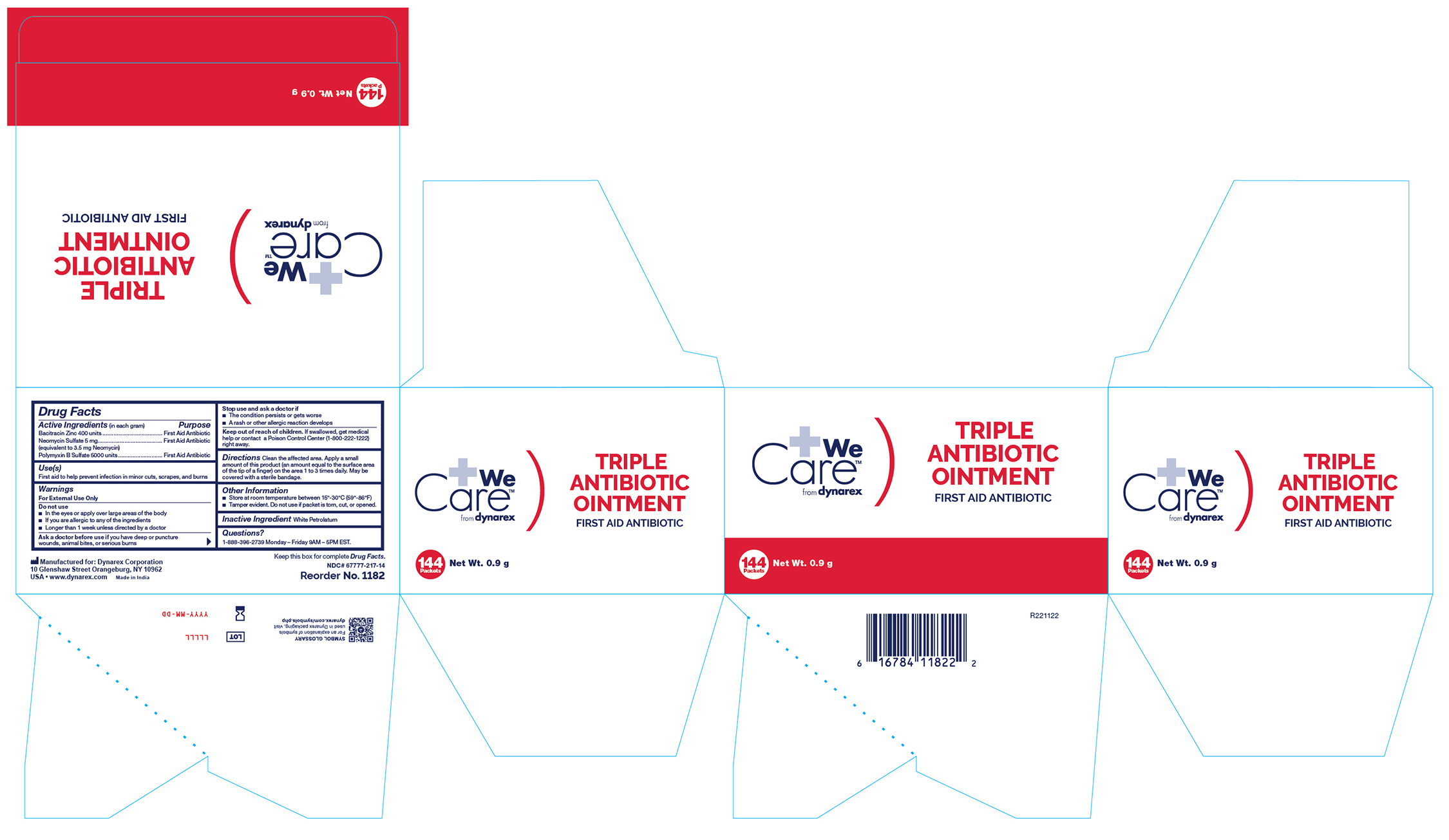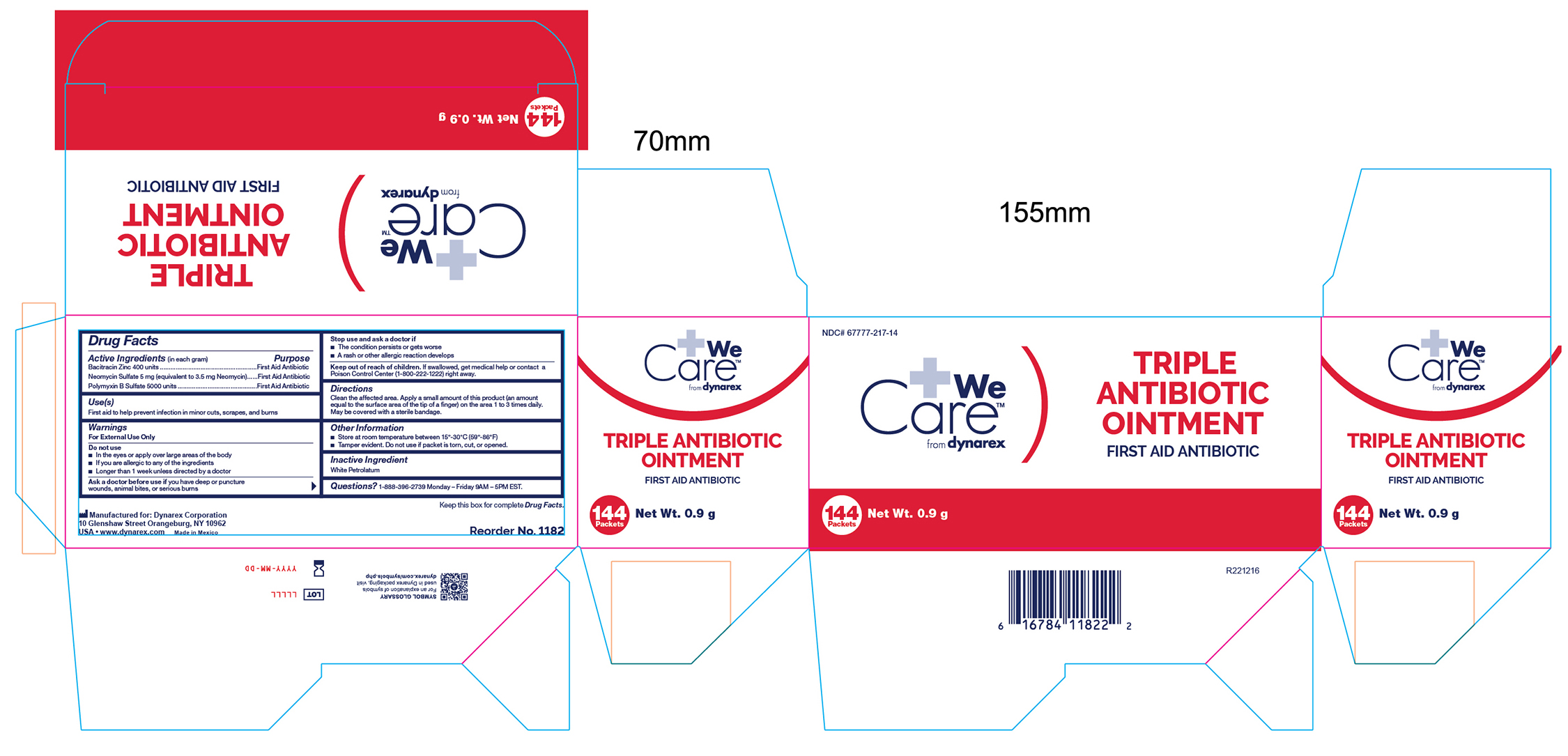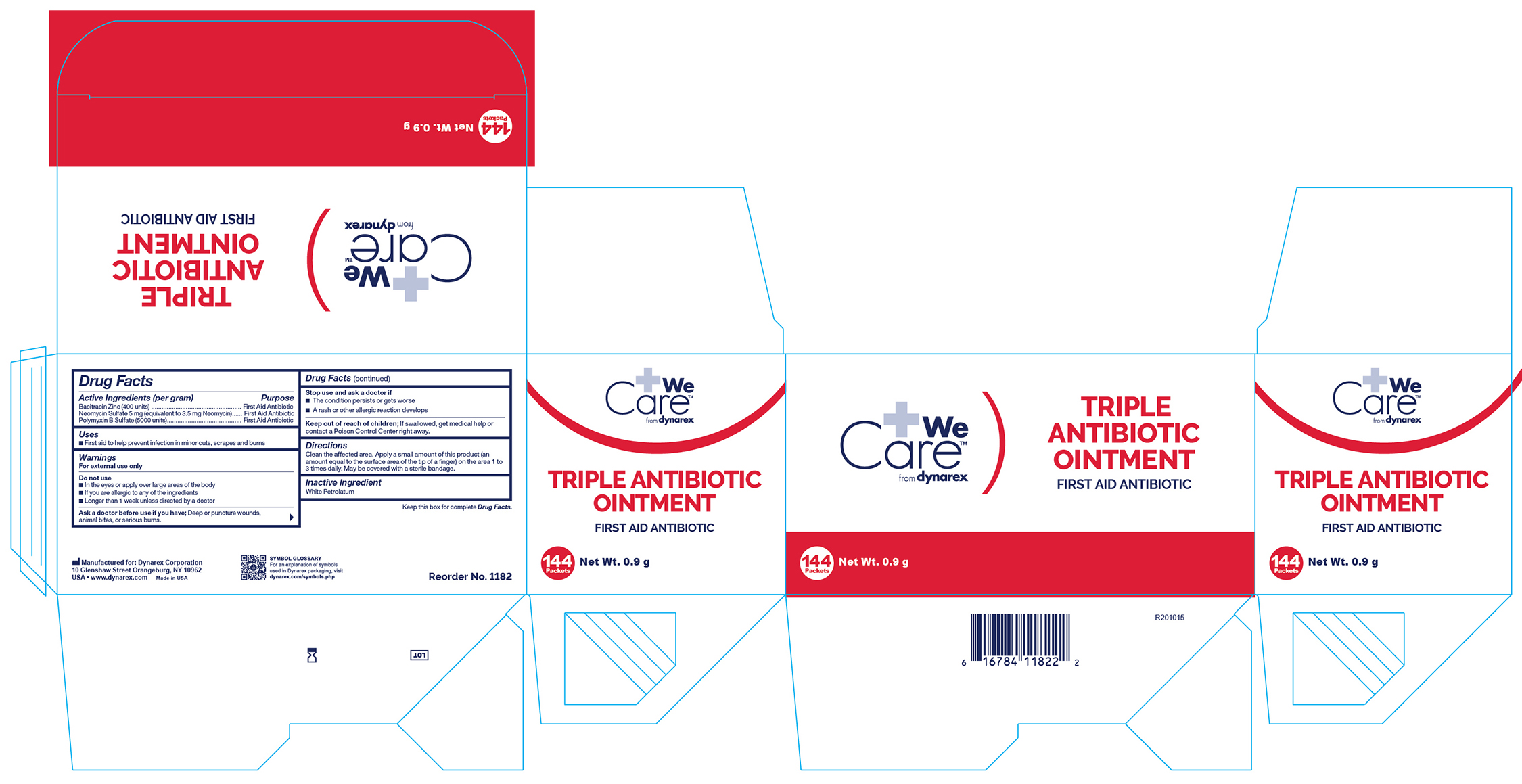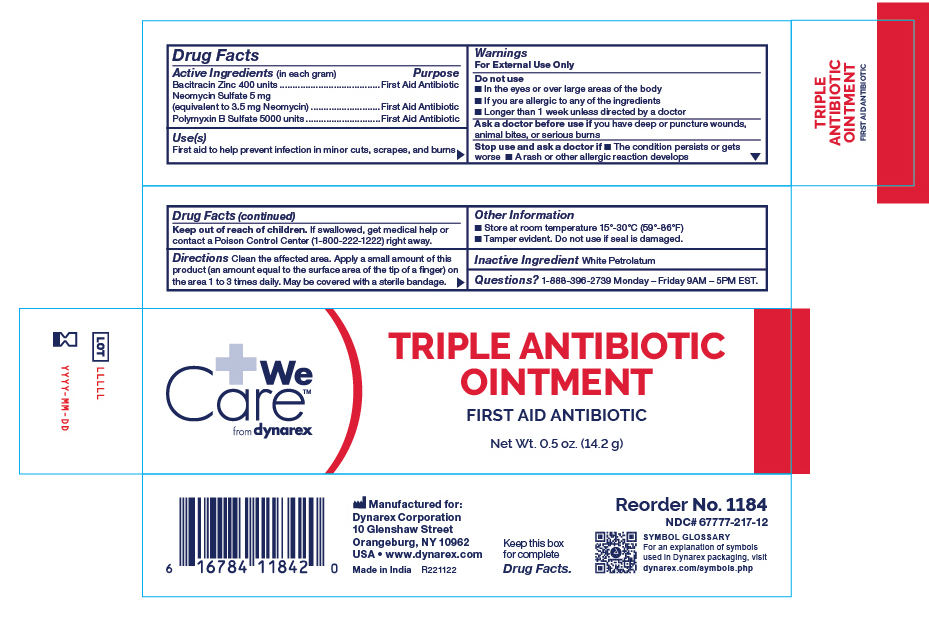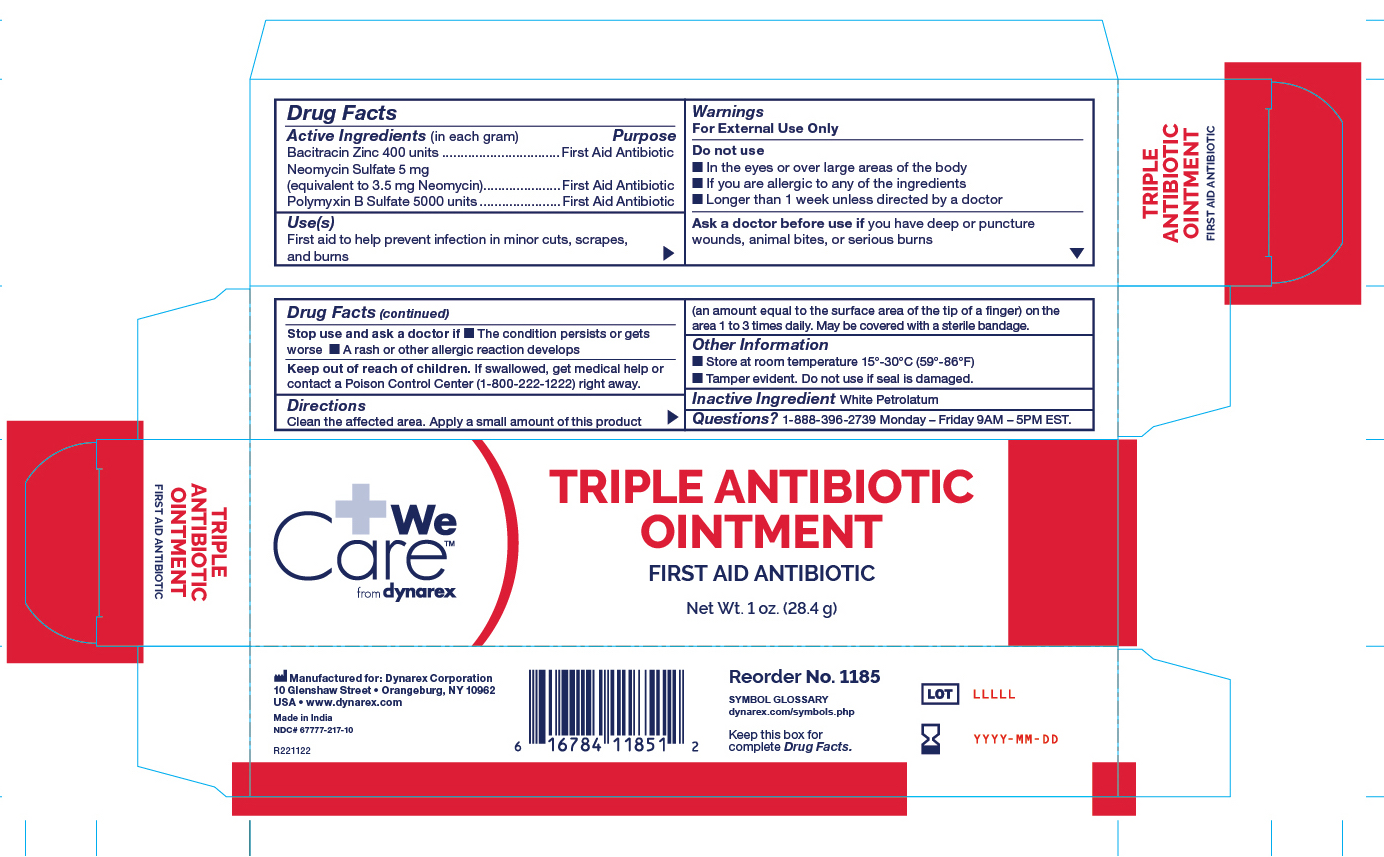 DRUG LABEL: bacitracin zinc, neomycin sulfate and polymyxin b sulfate
NDC: 67777-217 | Form: OINTMENT
Manufacturer: Dynarex Corporation
Category: otc | Type: HUMAN OTC DRUG LABEL
Date: 20250630

ACTIVE INGREDIENTS: BACITRACIN ZINC 400 [iU]/1 g; NEOMYCIN SULFATE 5 mg/1 g; POLYMYXIN B SULFATE 5000 [iU]/1 g
INACTIVE INGREDIENTS: WHITE PETROLATUM

1180 Triple Antibiotic Ointment 0.5 g NDC 67777-217-05, 1182 Triple Antibiotic Ointment 0.9 g NDC 67777-217-07
1184 Triple Antibiotic Ointment 14.17 g NDC 67777-217-02, 1185 Triple Antibiotic Ointment 28.35 g NDC 67777-217-01
1180UB-10 Triple Antibiotic Ointment 0.5 g NDC 67777-217

Active Ingredients (in each gram)

Bacitracin Zinc 400 Units

Neomyxin Sulfate 5mg (Equivalent to 3.5 mg Neomyxin)
Polymyxin B Sulfate 5000 Units

Purpose

First Aid Antibiotic

Use(s)

First aid to help prevent infection in minor cuts, scrapes, and burns

Warnings

For External Use Only

Do not use

• In the eyes or apply over large areas of the body

• If you are allergic to any of the ingredients

• Longer than 1 week unless directed by a doctor

Ask a doctor before use if

You have deep or puncture wounds, animal bites, or serious burns

Stop use and ask a doctor if

• The condition persists or gets worse

• A rash or other allergic reaction develops

Keep out of reach of children

If swallowed, get medical help or contact a Poison Control Center (1-800-222-1222) right away.

Directions

Clean the affected area. Apply a small amount of this product (an amount equal to the surface area of the tip of a finger) on the area 1 to 3 times daily. May be covered with a sterile bandage.

Other Information

• Store at room temperature between 15º-30ºC (59º-86ºF)

• Tamper evident. Do not use if packet is torn, cut, or opened.

Inactive Ingedient

White Petrolatum

Questions?

1-888-396-2739 Monday - Friday 9AM - 5PM EST

Label

Triple Antibiotic

Label 1180UB-10

1180UB-10